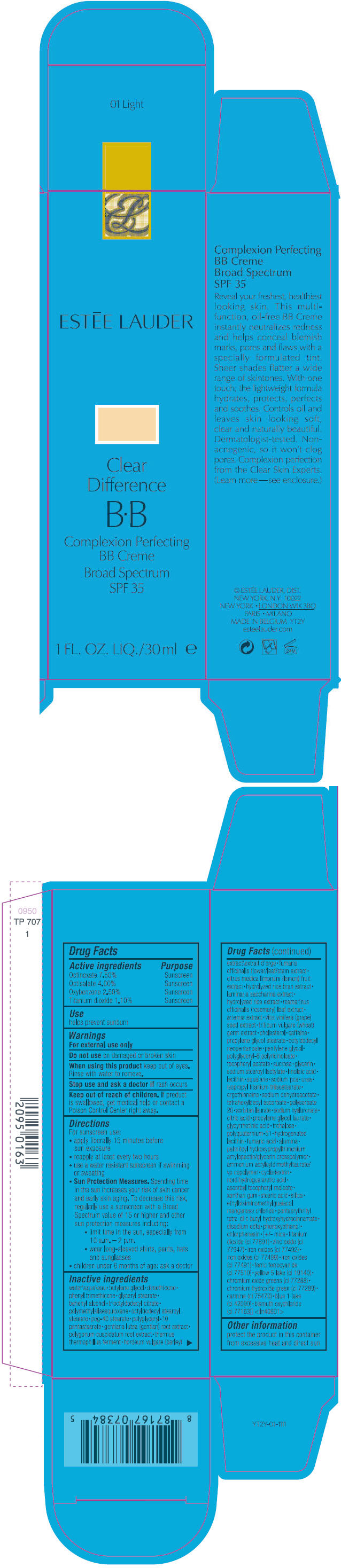 DRUG LABEL: CLEAR DIFFERENCE BB COMPLEXION PERFECTING BB BROAD SPECTRUM SPF 35
NDC: 11559-039 | Form: CREAM
Manufacturer: ESTEE LAUDER INC
Category: otc | Type: HUMAN OTC DRUG LABEL
Date: 20140117

ACTIVE INGREDIENTS: OCTINOXATE 0.08175 g/100 mL; OCTISALATE 0.0436 g/100 mL; OXYBENZONE 0.02725 g/100 mL; TITANIUM DIOXIDE 0.01199 g/100 mL
INACTIVE INGREDIENTS: water; 1,3-butylene glycol; dimethicone; phenyl trimethicone; GLYCERYL MONOSTEARATE; DOCOSANOL; trioctyldodecyl citrate; octyldodecyl stearoyl stearate; peg-40 stearate; GENTIANA LUTEA ROOT; POLYGONUM CUSPIDATUM ROOT; THERMUS THERMOPHILUS LYSATE; BARLEY; FUMARIA OFFICINALIS FLOWERING TOP; LEMON; SACCHARINA LATISSIMA; ROSEMARY; VITIS VINIFERA SEED; WHEAT GERM; cholesterol; caffeine; propylene glycol stearate; octyldodecyl neopentanoate; pentylene glycol; .ALPHA.-TOCOPHEROL ACETATE; sucrose; glycerin; sodium stearoyl lactylate; linoleic acid; squalane; SODIUM PYRROLIDONE CARBOXYLATE; urea; isopropyl titanium triisostearate; ergothioneine; sodium dehydroacetate; tetrahexyldecyl ascorbate; polysorbate 20; SORBITAN MONOLAURATE; HYALURONATE SODIUM; CITRIC ACID MONOHYDRATE; PROPYLENE GLYCOL MONOLAURATE; ENOXOLONE; trehalose; fumaric acid; ALUMINUM OXIDE; ammonium acryloyldimethyltaurate/vp copolymer; MASOPROCOL; ascorbyl tocopheryl maleate; xanthan gum; stearic acid; SILICON DIOXIDE; manganese chloride; PENTAERYTHRITOL TETRAKIS(3-(3,5-DI-TERT-BUTYL-4-HYDROXYPHENYL)PROPIONATE); EDETATE DISODIUM; phenoxyethanol; chlorphenesin; mica; ZINC OXIDE; FERRIC OXIDE YELLOW; FERROSOFERRIC OXIDE; FERRIC OXIDE RED; FERRIC FERROCYANIDE; FD&C YELLOW NO. 5; CHROMIC OXIDE; CHROMIUM HYDROXIDE GREEN; CARMINIC ACID; FD&C BLUE NO. 1; BISMUTH OXYCHLORIDE

CLEAR DIFFERENCE BB COMPLEXION PERFECTING BB CREME BROAD SPECTRUM SPF 35

Drug Facts

ACTIVE INGREDIENT

Active ingredients | Purpose
Octinoxate 7.50% | Sunscreen
Octisalate 4.00% | Sunscreen
Oxybenzone 2.50% | Sunscreen
Titanium dioxide 1.10% | Sunscreen

Use

helps prevent sunburn

Warnings

For external use only

Do not use on damaged or broken skin

When using this product keep out of eyes. Rinse with water to remove.

Stop use and ask a doctor if rash occurs

Keep out of reach of children. If product is swallowed, get medical help or contact a Poison Control Center right away.

Directions

For sunscreen use:

- apply liberally 15 minutes before sun exposure
- reapply at least every two hours
- use a water resistant sunscreen if swimming or sweating
- Sun Protection Measures. Spending time in the sun increases your risk of skin cancer and early skin aging. To decrease this risk, regularly use a sunscreen with a Broad Spectrum value of 15 or higher and other sun protection measures including:
  - limit time in the sun, especially from 10 a.m. – 2 p.m.
  - wear long-sleeved shirts, pants, hats and sunglasses
- children under 6 months of age: ask a doctor

Inactive ingredients

water\aqua\eau • butylene glycol • dimethicone • phenyl trimethicone • glyceryl stearate • behenyl alcohol • trioctyldodecyl citrate • polymethylsilsesquioxane • octyldodecyl stearoyl stearate • peg-40 stearate • polyglyceryl-10 pentastearate • gentiana lutea (gentian) root extract • polygonum cuspidatum root extract • thermus thermophillus ferment • hordeum vulgare (barley) extract\extrait d'orge • fumaria officinalis flower/leaf/stem extract • citrus medica limonum (lemon) fruit extract • hydrolyzed rice bran extract • laminaria saccharina extract • hydrolyzed rice extract • rosmarinus officinalis (rosemary) leaf extract • artemia extract • vitis vinifera (grape) seed extract • triticum vulgare (wheat) germ extract • cholesterol • caffeine • propylene glycol stearate • octyldodecyl neopentanoate • pentylene glycol • polyglyceryl-6 polyricinoleate • tocopheryl acetate • sucrose • glycerin • sodium stearoyl lactylate • linoleic acid • lecithin • squalane • sodium pca • urea • isopropyl titanium triisostearate • ergothioneine • sodium dehydroacetate • tetrahexyldecyl ascorbate • polysorbate 20 • sorbitan laurate • sodium hyaluronate • citric acid • propylene glycol laurate • glycyrrhetinic acid • trehalose • polyquaternium-51 • hydrogenated lecithin • fumaric acid • alumina • palmitoyl hydroxypropyltrimonium • amylopectin/glycerin crosspolymer • ammonium acryloyldimethyltaurate/vp copolymer • cyclodextrin • nordihydroguaiaretic acid • ascorbyl tocopheryl maleate • xanthan gum • stearic acid • silica • ethylbisiminomethylguaiacol manganese chloride • pentaerythrityl tetra-di-t-butyl hydroxyhydrocinnamate • disodium edta • phenoxyethanol • chlorphenesin • [+/- mica • titanium dioxide (ci 77891) • zinc oxide (ci 77947) • iron oxides (ci 77492) • iron oxides (ci 77499) • iron oxides (ci 77491) • ferric ferrocyanide (ci 77510) • yellow 5 lake (ci 19140) • chromium oxide greens (ci 77288) • chromium hydroxide green (ci 77289) • carmine (ci 75470) • blue 1 lake (ci 42090) • bismuth oxychloride (ci 77163)] <iln40601>

Other information

protect the product in this container from excessive heat and direct sun

PRINCIPAL DISPLAY PANEL - 30 ml Tube Carton

ESTĒE LAUDER

Clear
Difference

B•B

Complexion Perfecting
BB Creme
Broad Spectrum
SPF 35

1 FL. OZ. LIQ./30 ml e